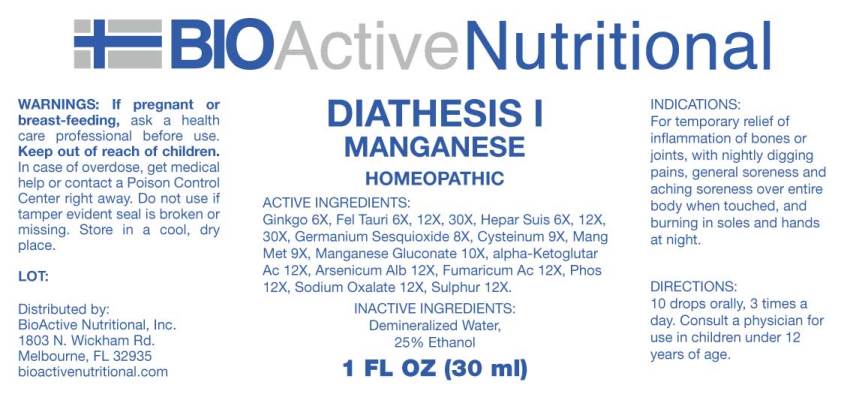 DRUG LABEL: Diathesis
NDC: 43857-0249 | Form: LIQUID
Manufacturer: BioActive Nutritionals, Inc.
Category: homeopathic | Type: HUMAN OTC DRUG LABEL
Date: 20180713

ACTIVE INGREDIENTS: MANGANESE 9 [hp_X]/1 mL; GERMANIUM SESQUIOXIDE 8 [hp_X]/1 mL; BOS TAURUS BILE 6 [hp_X]/1 mL; PORK LIVER 6 [hp_X]/1 mL; GINKGO 6 [hp_X]/1 mL; CYSTEINE 9 [hp_X]/1 mL; MANGANESE GLUCONATE 10 [hp_X]/1 mL; .ALPHA.-KETOGLUTARIC ACID 12 [hp_X]/1 mL; ARSENIC TRIOXIDE 12 [hp_X]/1 mL; FUMARIC ACID 12 [hp_X]/1 mL; PHOSPHORUS 12 [hp_X]/1 mL; SODIUM OXALATE 12 [hp_X]/1 mL; SULFUR 12 [hp_X]/1 mL
INACTIVE INGREDIENTS: WATER; ALCOHOL

Drug Facts:

ACTIVE INGREDIENTS:

Manganum Metallicum 9X, Germanium Sesquioxide 8X, Fel Tauri (Ox) 6X, 12X, 30X, Hepar Suis 6X, 12X, 30X, Ginkgo Biloba 6X, Cysteinum 9X, Manganese Gluconate 10X, alpha-Ketoglutaricum Acidum 12X, Arsenicum Album 12X, Fumaricum Acidum 12X, Phosphorus 12X, Sodium Oxalate 12X, Sulphur 12X.

INDICATIONS:

For temporary relief of inflammation of bones or joints, with nightly digging pains, general soreness and aching soreness over entire body when touched, and burning in soles and hands at night.

WARNINGS:

If pregnant or breast-feeding, ask a health care professional before use.

Keep out of reach of children. In case of overdose, get medical help or contact a Poison Control Center right away.

Do not use if tamper evident seal is broken or missing.

Store in a cool, dry place.

Keep out of reach of children. In case of overdose, get medical help or contact a Poison Control Center right away.

DIRECTIONS:

10 drops orally, 3 times a day. Consult a physician for use in children under 12 years of age.

INDICATIONS:

For temporary relief of inflammation of bones or joints, with nightly digging pains, general soreness and aching soreness over entire body when touched, and burning in soles and hands at night.

INACTIVE INGREDIENTS:

Demineralized Water, 25% Ethanol

QUESTIONS:

Distributed by:
BioActive Nutritional, Inc.
1803 N. Wickham Rd.
Melbourne, FL 32935
bioactivenutritional.com

PACKAGE LABEL DISPLAY:

BIOActive Nutritional

DIATHESIS I

HOMEOPATHIC

1 FL OZ (30 ml)